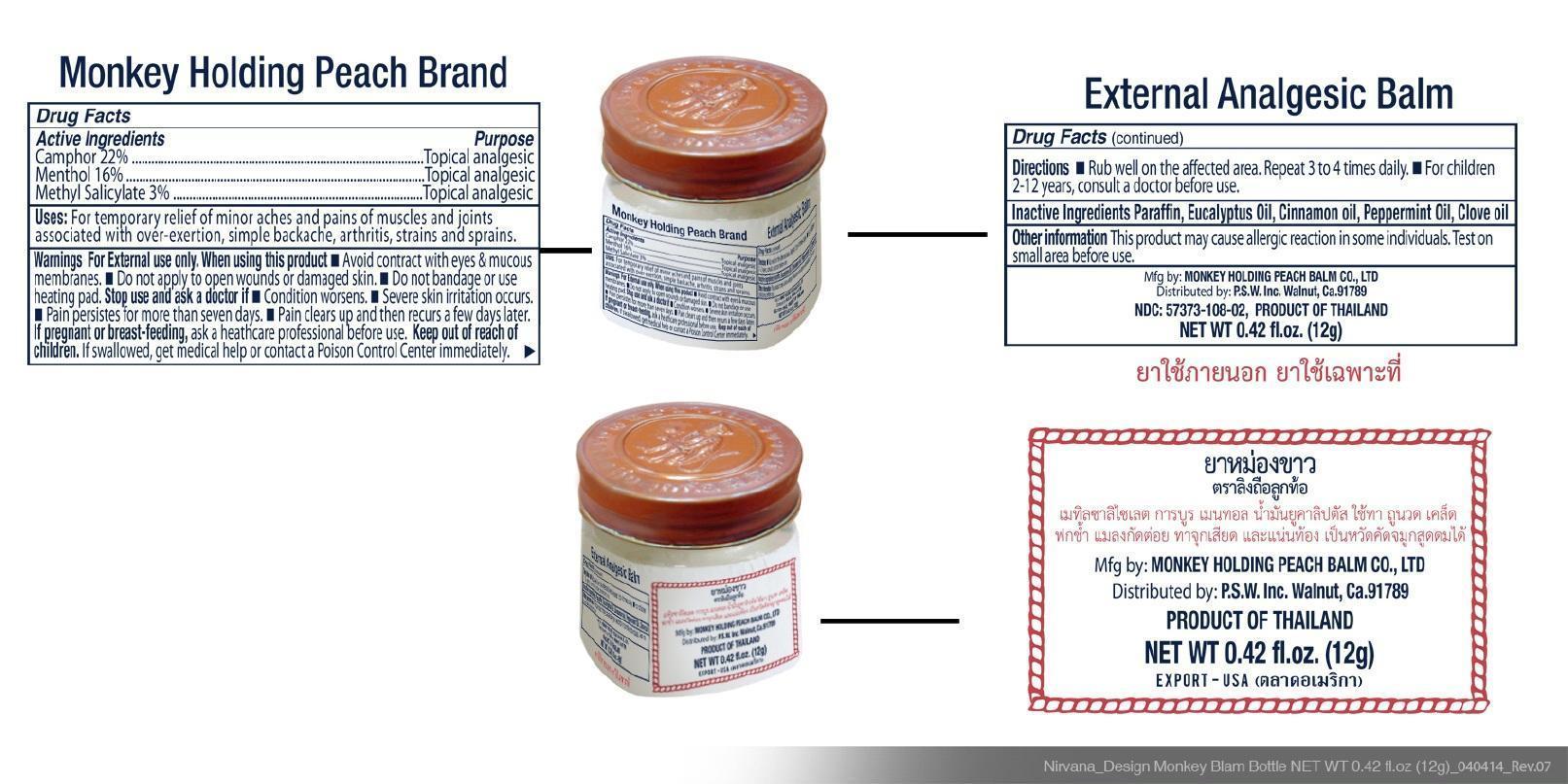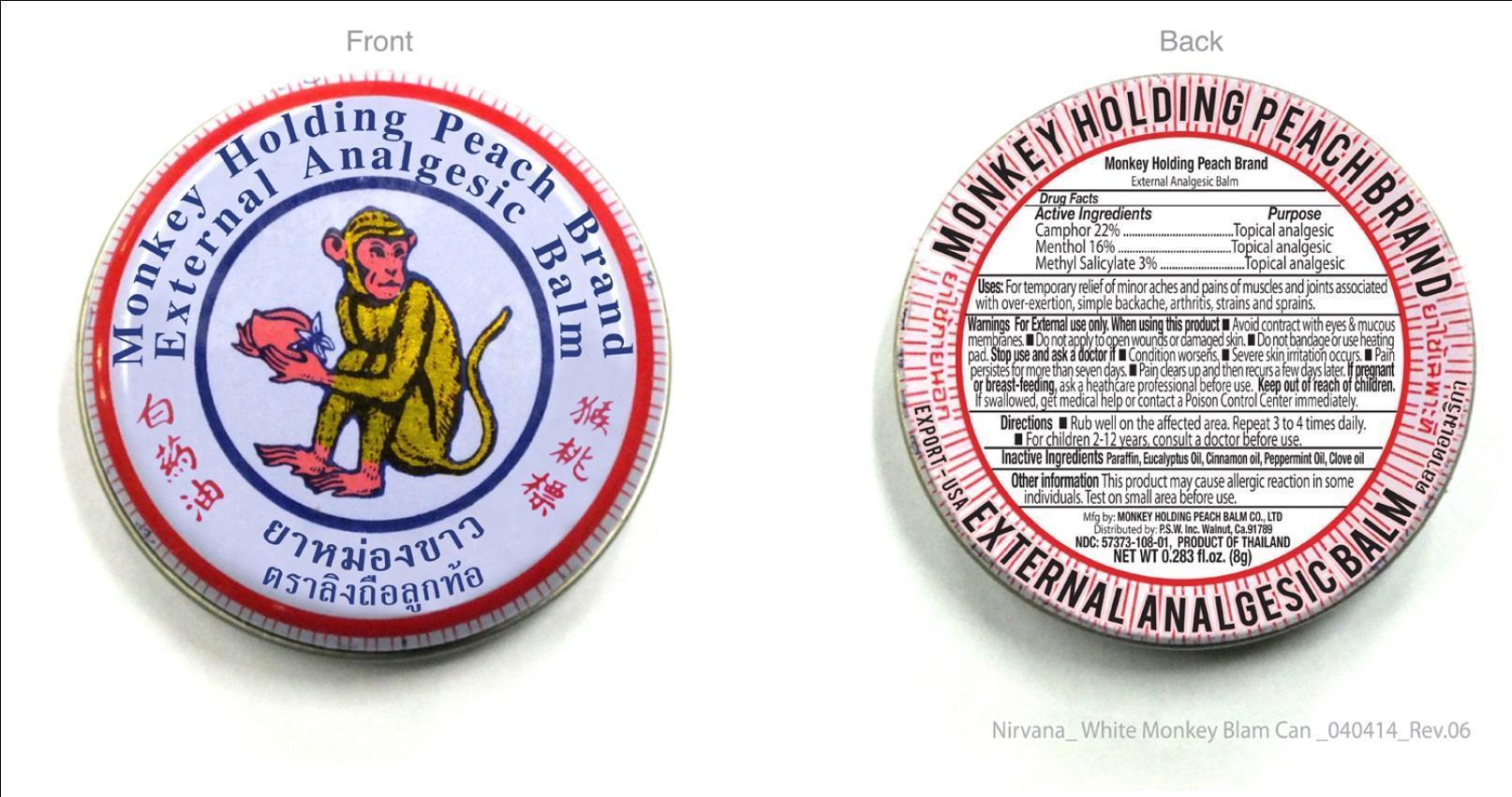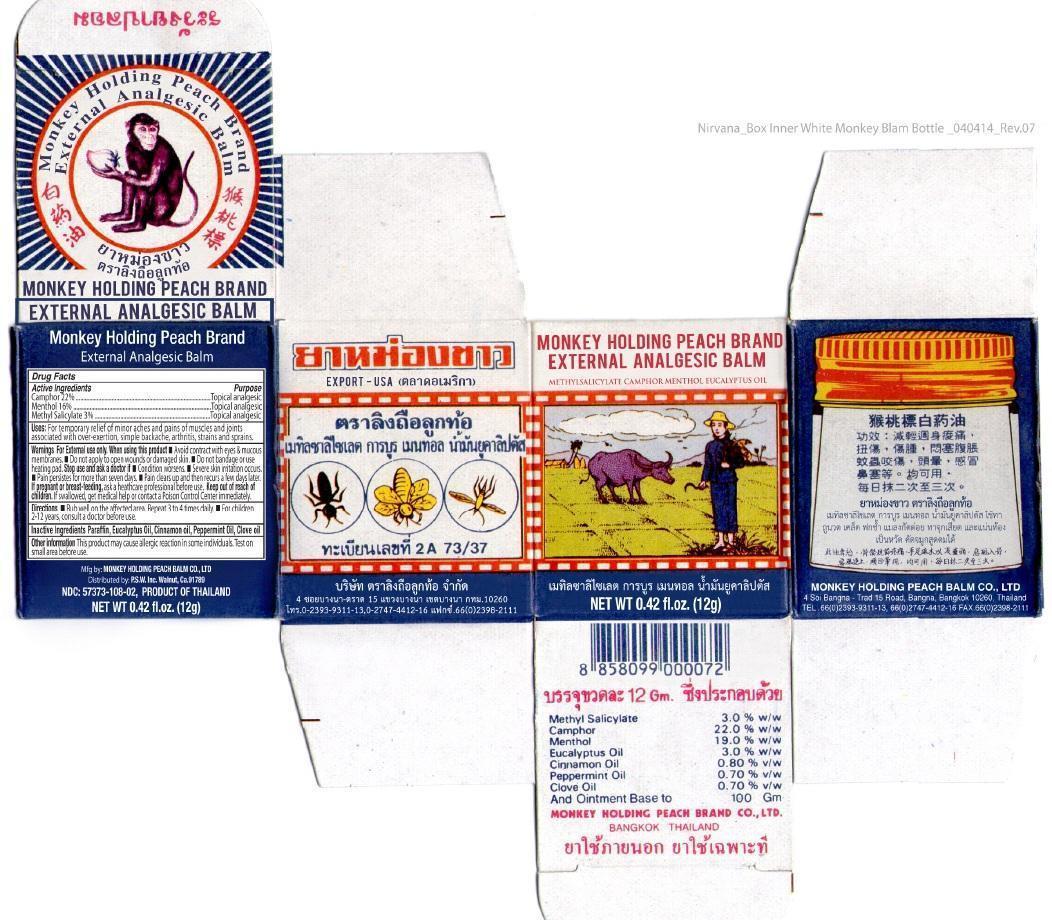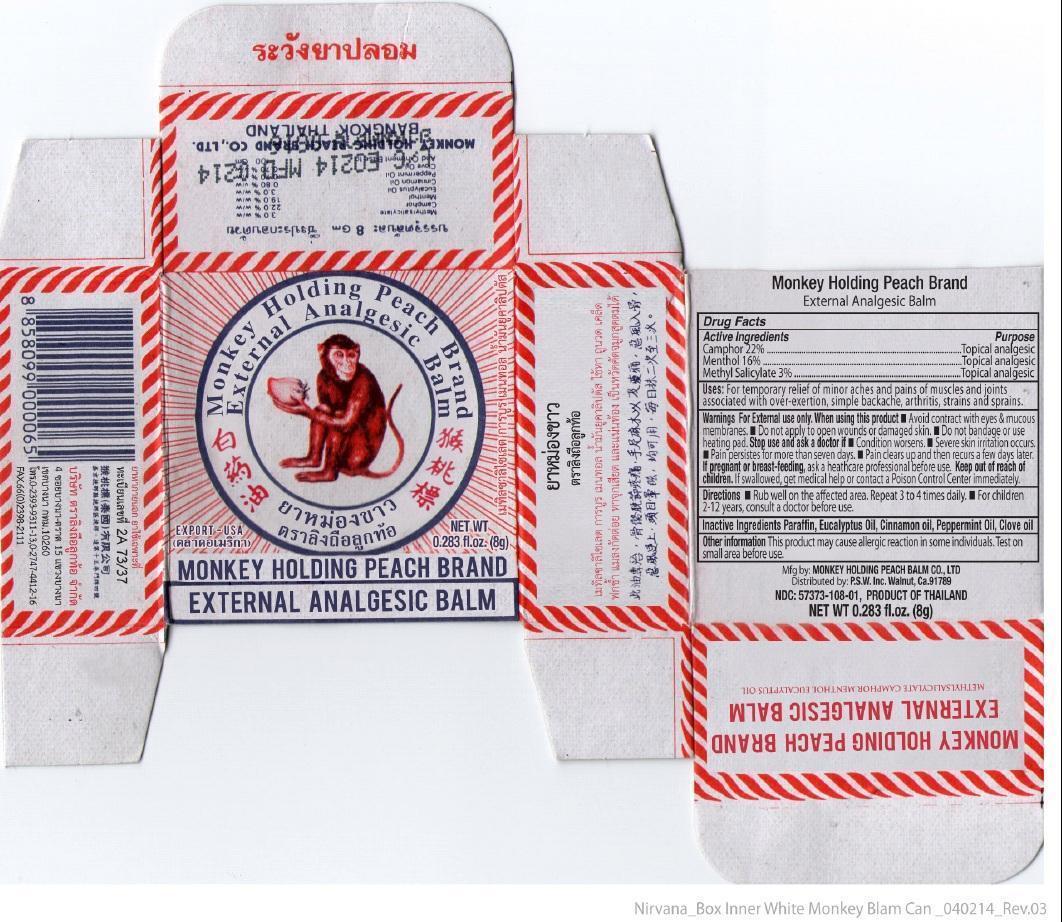 DRUG LABEL: Monkey Holding Peach Brand
NDC: 57373-108 | Form: OINTMENT
Manufacturer: P.S.W. INC.
Category: otc | Type: HUMAN OTC DRUG LABEL
Date: 20140414

ACTIVE INGREDIENTS: CAMPHOR (NATURAL) 22 g/100 g; MENTHOL 16 g/100 g; METHYL SALICYLATE 3 g/100 g
INACTIVE INGREDIENTS: PARAFFIN; EUCALYPTUS OIL; CINNAMON OIL; PEPPERMINT OIL; CLOVE OIL

Drug Facts

Active Ingredients

Camphor 22%

Menthol 16%

Methyl Salicylate 3%

Purpose

Topical Analgesic

Uses

For temporary relief of minor aches and pains of muscles and joints associated with over-exertion, simple backache, arthritis, strains and sprains.

Directions

- Rub well on the affected area. Repeat 3 to 4 times daily.
- For children 2-12 years, consult a doctor before use.

Inactive Ingredients

Paraffin, Eucalyptus Oil, Cinnamon Oil, Peppermint Oil, Olive Oil.

Warnings

For External Use Only.

When using this product

- Avoid contact with eyes or mucous membranes.
- Do not apply to open wounds or damaged skin.
- Do not bandage or use heating pad.

Stop use and ask a doctor

- Condition worsens
- Severe skin irritation occurs
- Pain persistes for more than seven days.
- Pain clears up and then recurs a few days later

If pregnant or breast-feeding

ask a healthcare professional before use.

Keep out of reach of children

If swallowed, get medical help or contact a Poison Control Center immediately.

Other information

This product may cause allergic reaction in some individuals. test on small area before use.

Principal Display Panel

Monkey Holding Peach Brand External Analgesic Balm

Export USA

Net Wt. 0.283 fl.oz. (8g)

NDC 57373-108-01

Product of Thailand

MONKEY HOLDING PEACH BALM EXTERNAL ANALGESIC BALM

Methyl Salicylate Camphor Menthol Eucalyptus Oil

Net Wt. 0.42 fl.oz. (12g)

NDC 57373-108-02

Product of Thailand